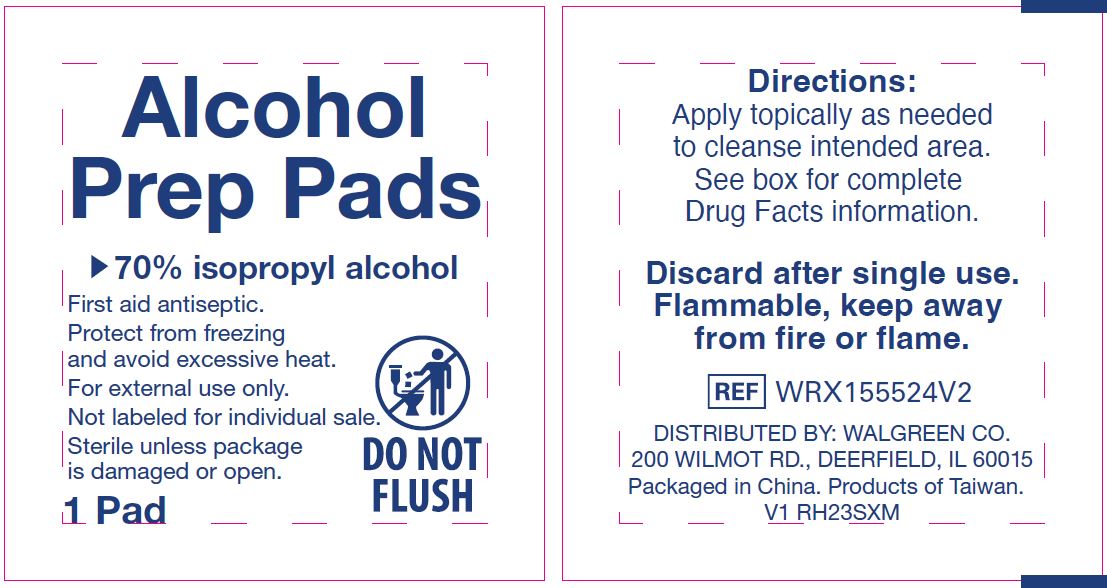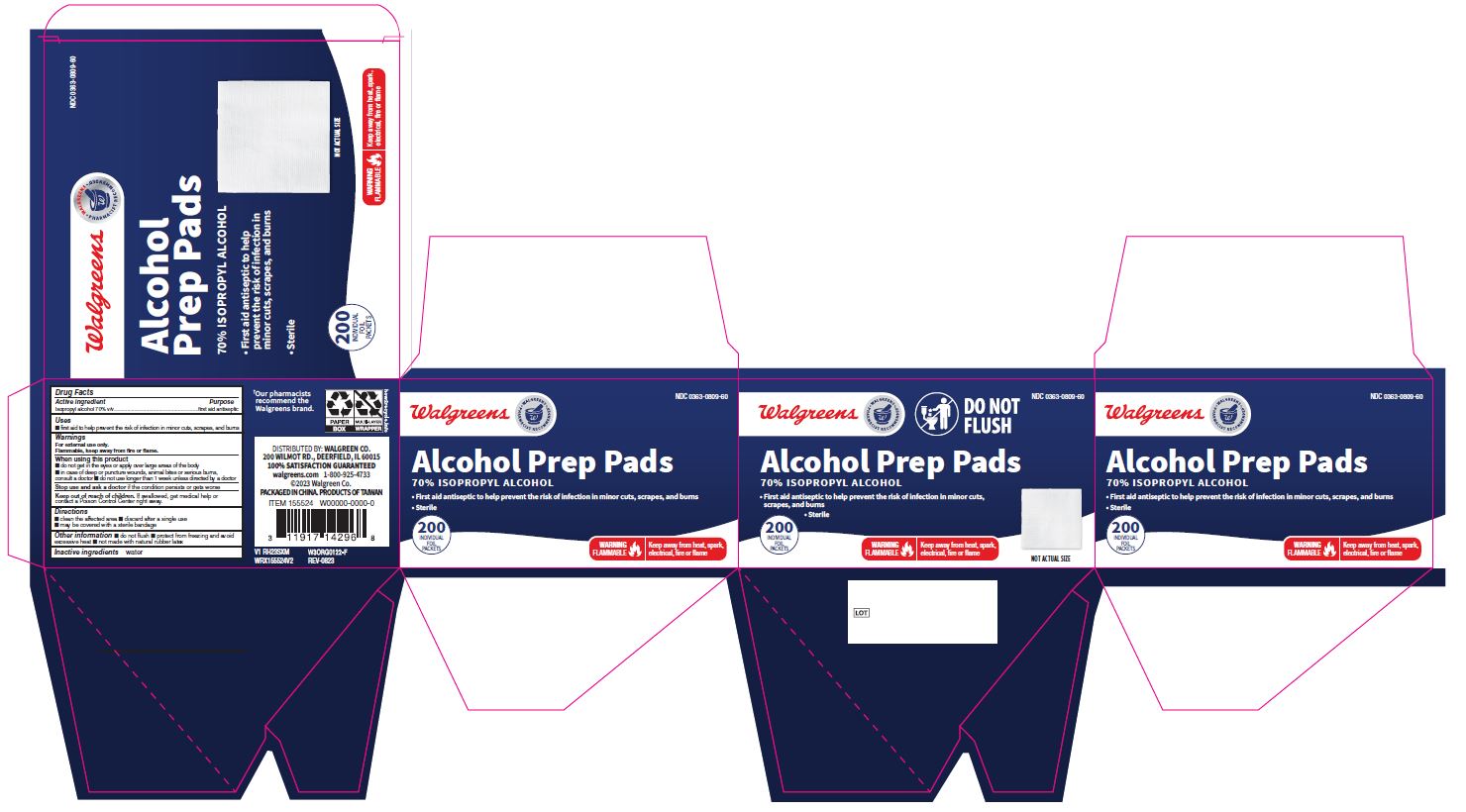 DRUG LABEL: Walgreen Alcohol
NDC: 0363-0809 | Form: SWAB
Manufacturer: Walgreens Company
Category: otc | Type: HUMAN OTC DRUG LABEL
Date: 20250102

ACTIVE INGREDIENTS: ISOPROPYL ALCOHOL 70 mL/100 mL
INACTIVE INGREDIENTS: WATER

0363-0809 Walgreens IPA Pads

Active ingredient

Isopropyl alcohol 70% v/v

Purpose

First aid antiseptic

Use

- first aid to decrease germs in minor cuts, scrapes and burns

Warnings

For external use only.

Flammable, keep away from fire or flame.

When using this product

- do not get in the eyes or apply over large areas of the body
- in case of deep or puncture wounds, animal bites or serious burns, consult a doctor
- do not use longer than 1 week unless directed by a doctor

Stop use and ask a doctor if

- the condition persists or gets worse

Keep out of reach of children.

If swallowed, get medical help or contact a Poison Control Center right away.

Directions

- clean the affected area
- discard after a single use
- may be covered with a sterile bandage

Other information

- do not flush
- protect from freezing and avoid excessive heat
- not made with natural rubber latex

Inactive ingredients

water

Manufacturing Information

Questions or comments?

1-800-633-5463

Distributed by: Walgreen Co.

200 Wilmot Rd., Deerfield, IL 60015

walgreens.com

Made in China

WRX155524V2

V1 RH23SXM